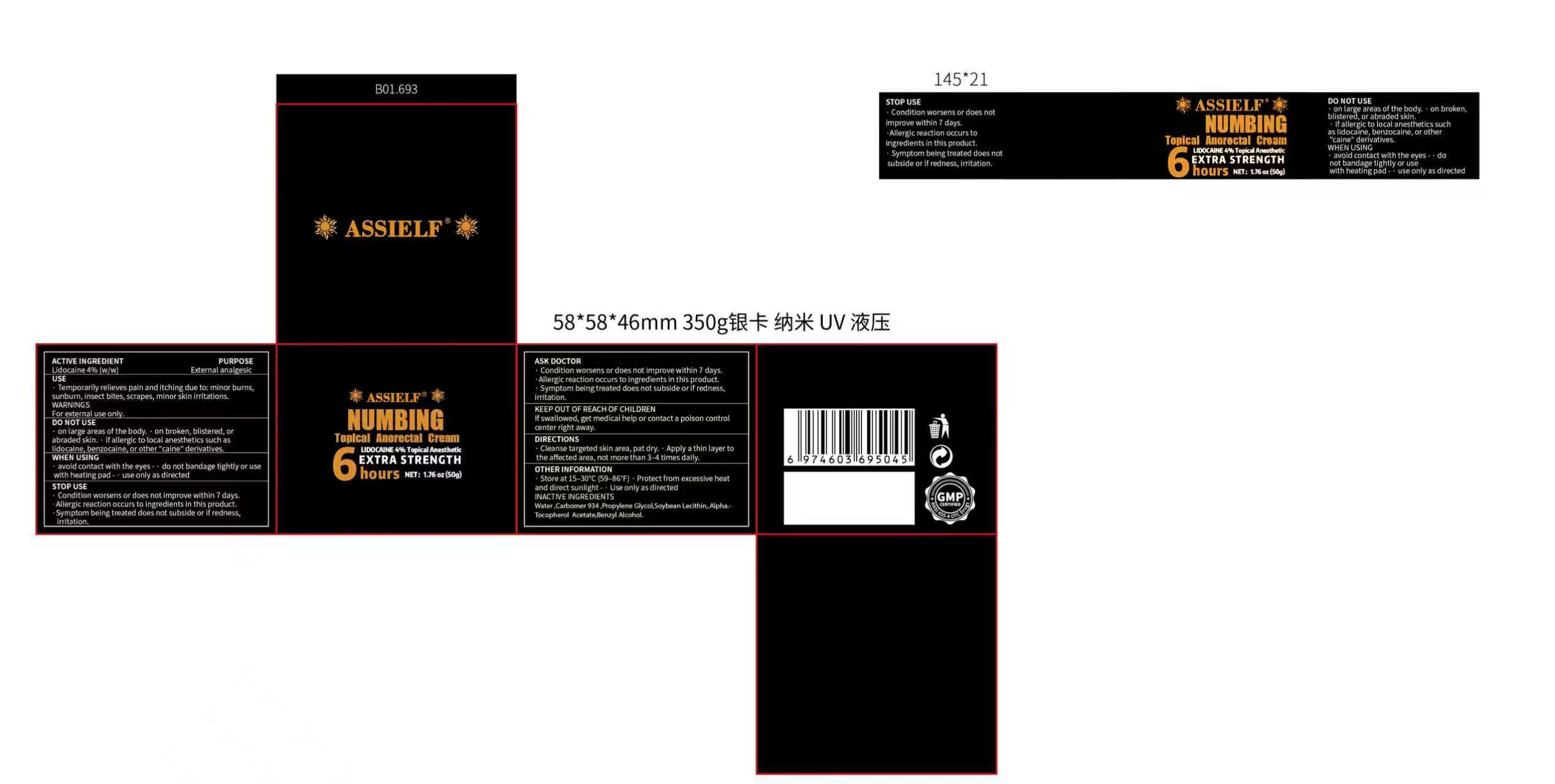 DRUG LABEL: ASSIELF NUMBING Topical Anorectal
NDC: 87418-001 | Form: CREAM
Manufacturer: Shenzhen Yuanbang International Logistics Co., Ltd
Category: otc | Type: HUMAN OTC DRUG LABEL
Date: 20260208

ACTIVE INGREDIENTS: LIDOCAINE 4 g/100 g
INACTIVE INGREDIENTS: WATER; CARBOMER 934; SOYBEAN LECITHIN; BENZYL ALCOHOL; PROPYLENE GLYCOL; ALPHA-TOCOPHEROL ACETATE

87418-001-01 ASSIELF NUMBING Topical Anorectal Cream

ACTIVE INGREDIENT

Lidocaine 4% (w/w)

PURPOSE

Temporarily relieves pain and itching due to: minor burns,sunburn, insect bites, scrapes, minor skin irritations

KEEP OUT OF REACH OF CHILDREN
If swallowed, get medical help or contact a poison control
center right away.

DIRECTIONS
Cleanse targeted skin area, pat dry. Apply a thin layer tothe affected area, not more than 3-4 times daily.

INDICATIONS AND USAGE

Condition worsens or does not improve within 7 days.Allergic reaction occurs to ingredients in this product.Symptom being treated does not subside or if redness,irritation.

INACTIVE INGREDIENT

Water,Carbomer 934,Propylene Glycol,Soybean Lecithin, AlphTocopherol Acetate,Benzyl Alcohol.

DO NOT USE
on large areas of the body. on broken, blistered, orabraded skin. if allergic to local anesthetics such aslidocaine, benzocaine, or other"caine" derivatives.WHEN USINGavoid contact with the eyes- do not bandage tightly or usewith heating pad - use only as directed